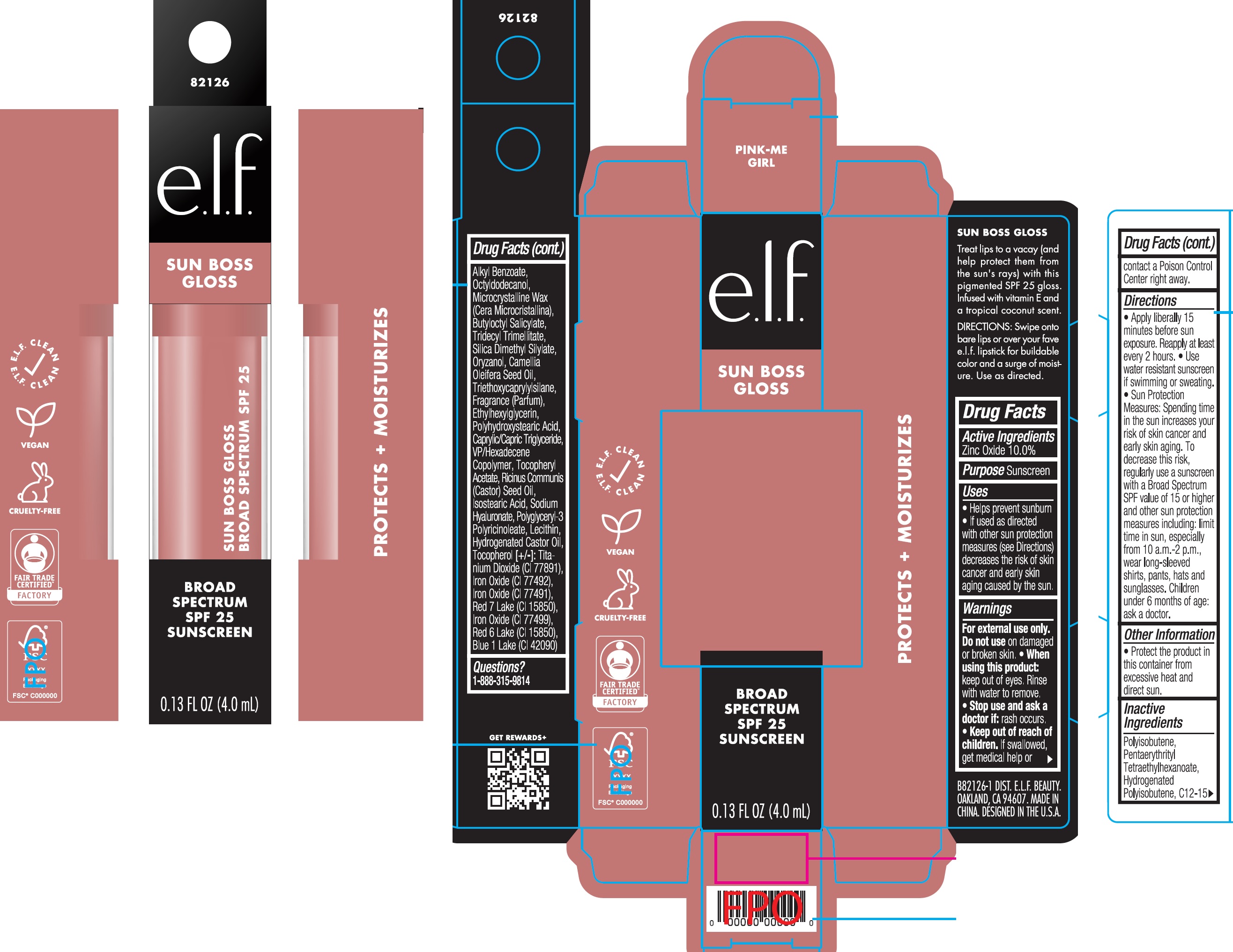 DRUG LABEL: elf Sun Boss Gloss SPF 25 Sunscreen Pink Me Girl
NDC: 76354-126 | Form: CREAM
Manufacturer: e.l.f. Cosmetics, Inc.
Category: otc | Type: HUMAN OTC DRUG LABEL
Date: 20251204

ACTIVE INGREDIENTS: ZINC OXIDE 100 mg/1 mL
INACTIVE INGREDIENTS: PENTAERYTHRITYL TETRAETHYLHEXANOATE; ALKYL (C12-15) BENZOATE; OCTYLDODECANOL; MICROCRYSTALLINE WAX; BUTYLOCTYL SALICYLATE; TRIDECYL TRIMELLITATE; SILICA DIMETHYL SILYLATE; ORYZANOL; CAMELLIA OIL; TRIETHOXYCAPRYLYLSILANE; ETHYLHEXYLGLYCERIN; MEDIUM-CHAIN TRIGLYCERIDES; VINYLPYRROLIDONE/HEXADECENE COPOLYMER; .ALPHA.-TOCOPHEROL ACETATE; CASTOR OIL; ISOSTEARIC ACID; HYALURONATE SODIUM; HYDROGENATED CASTOR OIL; TOCOPHEROL; TITANIUM DIOXIDE; FERRIC OXIDE YELLOW; FERRIC OXIDE RED; D&C RED NO. 6; FERROSOFERRIC OXIDE; FD&C BLUE NO. 1

e.l.f Sun Boss Gloss SPF 25 Sunscreen Pink-Me Girl

Active Ingredients

Zinc Oxide 10.0%

Purpose

Sunscreen

Uses

- Helps prevent sunburn
- If used as directed with other sun protection measures (see Directions) decreases the risk of skin cancer and early skin aging caused by the sun.

Warnings

For external use only.

Do not use

- on damaged or broken skin.

When using this product:

- keep out of eyes. Rinse with water to remove.

Stop use and ask a doctor if:

- rash occurs.

Keep out of reach of children.

- If swallowed, get medical help or contact a Poison Control Center right away.

Directions

- Apply liberally 15 minutes before sun exposure. Reapply at least every 2 hours.
- Use water resistant sunscreen if swimming or sweating.
- Sun Protection Measures: Spending time in the sun increases your risk of skin cancer and early skin aging. To decrease this risk, regularly use a sunscreen with a Board Spectrum SPF value of 15 or higher and other sun protection measures including: limit time in sun, especially from 10 a.m.-2 p.m., wear long-sleeved shirts, pants, hats and sunglasses. Children under 6 months of age: ask a doctor.

Other Information

- Protect the product in this container from excessive heat and direct sun.

Inactive Ingredients

Polyisobutene, Pentaerythrityl Tetraethylhexanoate, Hydrogenated Polysiobutene, C12-15 Alkyl Benzoate, Octyldodecanol, Microcrystalline Wax (Cera Microcristallina), Butyloctyl Salicylate, Tridecyl Trimellitate, Silica Dimethyl Silylate, Oryzanol, Camellia Oleifera Seed Oil, Triethoxycaprylylsilane, Fragrance (Parfum), Ethylhexylglycerin, Polyhydroxystearic Acid, Caprylic/Capric Triglyceride, VP/Hexadecene Copolymer, Tocopheryl Acetate, Ricinus Communis (Castor) Seed Oil, Isostearic Acid, Sodium Hyaluronate, Polyglyceryl-3 Polyricinoleate, Lecithin, Hydrogenated Castor Oil, Tocopherol [+/-]: Titanium Dioxide (CI 77891), Iron Oxide (CI 77492), Iron Oxide (CI 77491), Red 7 Lake (CI 15850), Iron Oxide (CI 77499), Red 6 Lakes (CI 15850), Blue 1 Lake (CI 42090)

Questions?

1-888-315-9814